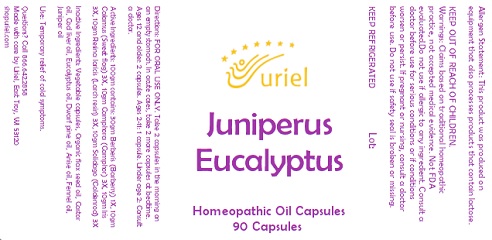 DRUG LABEL: Juniperus Eucalyptus
NDC: 48951-6082 | Form: CAPSULE, LIQUID FILLED
Manufacturer: Uriel Pharmacy, Inc.
Category: homeopathic | Type: HUMAN OTC DRUG LABEL
Date: 20230911

ACTIVE INGREDIENTS: LARIX DECIDUA RESIN 3 [hp_X]/1 1; CAMPHOR (NATURAL) 3 [hp_X]/1 1; ACORUS CALAMUS ROOT 3 [hp_X]/1 1; BERBERIS VULGARIS ROOT BARK 1 [hp_X]/1 1; C12-17 ALKANE 3 [hp_X]/1 1; SOLIDAGO VIRGAUREA FLOWERING TOP 3 [hp_X]/1 1
INACTIVE INGREDIENTS: PINE NEEDLE OIL (PINUS MUGO); ANISE OIL; JUNIPERUS OXYCEDRUS LEAF OIL; LINSEED OIL; POWDERED CELLULOSE; CASTOR OIL; COD LIVER OIL; EUCALYPTUS OIL; FENNEL OIL

Juniperus Eucalyptus

INDICATIONS AND USAGE

Directions: FOR ORAL USE ONLY.

DOSAGE AND ADMINISTRATION

Take 2 capsules in the morning on an empty stomach. In acute cases, take 2 more capsules at bedtime. Ages 12 and older: 2 capsules. Ages 2-11: 1 capsule. Under age 2: Consult a doctor.

ACTIVE INGREDIENT

Active Ingredients: 100gm contains: 30gm Berberis (Barberry) 1X, 10gm Calamus (Sweet flag) 3X, 10gm Camphora (Camphor) 3X, 10gm Iris 3X, 10gm Resina laricis (Larch resin) 3X, 10gm Solidago (Goldenrod) 3X

INACTIVE INGREDIENT

Inactive Ingredients: Vegetable capsules, Organic flax seed oil, Castor oil, Cod liver oil, Eucalyptus oil, Dwarf pine oil, Anise oil, Fennel oil, Juniper oil

PURPOSE

Use: Temporary relief of cold symptoms.

KEEP OUT OF REACH OF CHILDREN.

WARNINGS

Warnings: Claims based on traditional homeopathic practice, not accepted medical evidence.
Not FDA evaluated.Do not use if allergic to any ingredient. Consult a doctor before use for serious conditions or if conditions worsen or persist. If pregnant or nursing, consult a doctor before use. Do not use if safety seal is broken or missing.

KEEP REFRIGERATED

Questions? Call 866.642.2858
Made with care by Uriel, East Troy, WI 53120
shopuriel.com Lot: